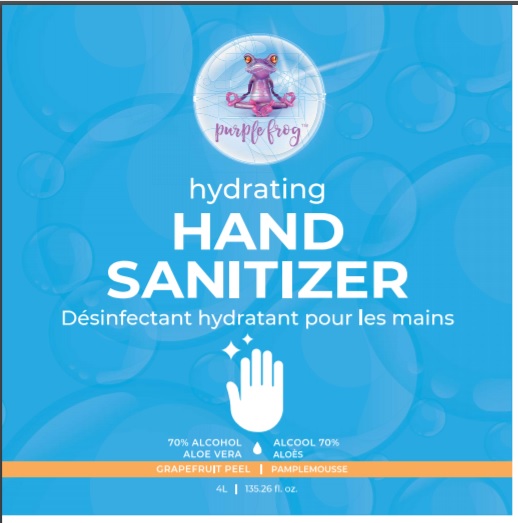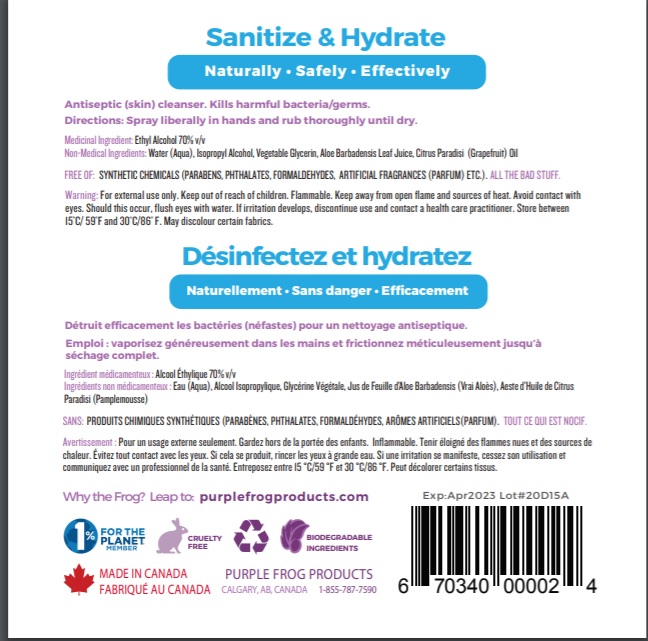 DRUG LABEL: Purple Frog Hand Sanitizer
NDC: 50157-338 | Form: GEL
Manufacturer: Brands International
Category: otc | Type: HUMAN OTC DRUG LABEL
Date: 20200502

ACTIVE INGREDIENTS: ALCOHOL 0.7 mL/1 mL
INACTIVE INGREDIENTS: WATER; ISOPROPYL ALCOHOL; ALOE VERA LEAF; CITRUS PARADISI FRUIT OIL; .ALPHA.-TOCOPHEROL ACETATE, D-; GLYCERIN

Purple Frog Hand Sanitizer

Active Ingredients

Ethyl Alcohol 70%v/v.

Purpose: Antiseptic

Purpose

Antiseptic

Safety Instructions

Flammable, Keep away from fire and flame

Ask Doctor

Stop Use and Ask a doctor if irritation or redness develops

KEEP OUT OF REACH OF CHILDREN

If swallowed, get medical help or contact Poison Control right away

Other Information

Store below 110°F (43°C)
May discolor certain fabrics or surfaces.

Inactive Ingredients

water, isopropyl alcohol, glycerin, carbomer, aminomethyl propanol, fragrance, propylene glycol, isopropyl myristate, propylene glycol, Aloe, Tocopheryl Acetate.

Directions

- Place enough product in your palm to thoroughly cover your hands
- Rub hands together briskly until dry
- Children under 6 years of age should be supervised when using this product.

Warnings

For external use only.

Flammable. Keep away from fire or flame.

Uses

- helps reduce bacteria on the skin that could cause disease